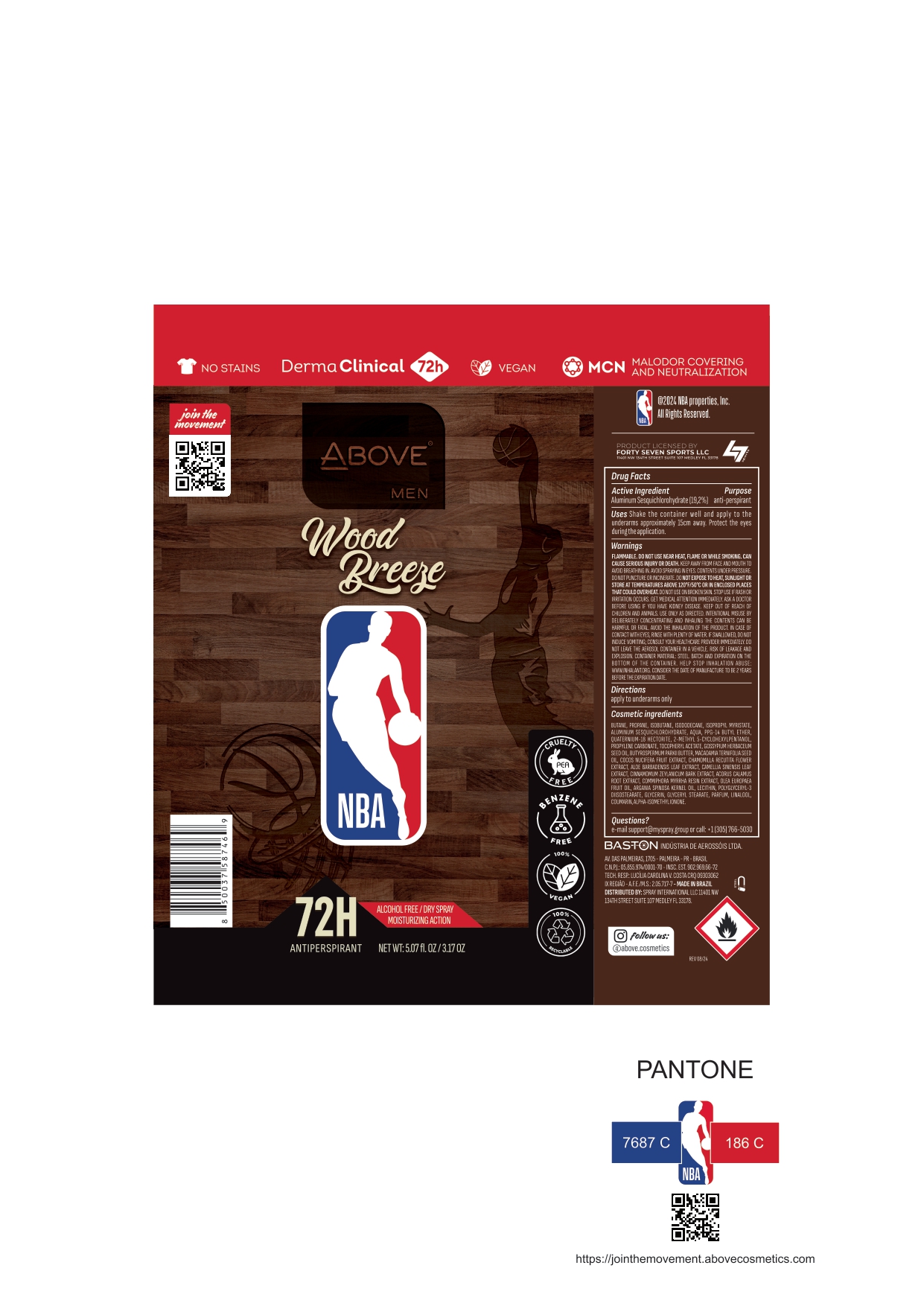 DRUG LABEL: ABOVE NBA MEN WOOD BREEZE  ANTIPERSPIRANT DEODORANT 72H
NDC: 73306-1164 | Form: AEROSOL, SPRAY
Manufacturer: BASTON INDUSTRIA DE AEROSSOIS LTDA
Category: otc | Type: HUMAN OTC DRUG LABEL
Date: 20241009

ACTIVE INGREDIENTS: ALUMINUM SESQUICHLOROHYDRATE 19.2 mg/100 g
INACTIVE INGREDIENTS: ISOBUTANE

ABOVE NBA MEN WOOD BREEZE ANTIPERSPIRANT DEODORANT 72H SPRAY

INACTIVE INGREDIENT

BUTANE (BUTANO)
PROPANE (PROPANO)
ISOBUTANE (ISOBUTANO)
ISOPROPYL MYRISTATE (MIRISTATO DE ISOPROPILA)
ISODODECANE (ISODODECANO)
AQUA (ÁGUA)
PPG-14 BUTYL ETHER (ÉTER BUTÍLICO PPG-14)
PARFUM (PERFUME)
QUATERNIUM-18 HECTORITE (QUATÉRNIO-18 HECTORITA)
2-METHYL 5-CYCLOHEXYLPENTANOL (2-METIL 5-CICLOEXILPENTANOL)
PROPYLENE CARBONATE (CARBONATO DE PROPILENO)
TOCOPHERYL ACETATE (ACETATO DE DEXTROALFATOCOFEROL)
GOSSYPIUM HERBACEUM SEED OIL (ÓLEO DA SEMENTE DE ALGODOEIRO)
BUTYROSPERMUM PARKII BUTTER (MANTEIGA DE KARITÉ)
MACADAMIA TERNIFOLIA SEED OIL (ÓLEO DA SEMENTE DE MACADÂMIA)
COCOS NUCIFERA FRUIT EXTRACT (EXTRATO DO FRUTO DE COQUEIRO)
CHAMOMILLA RECUTITA FLOWER EXTRACT (EXTRATO DA FLOR DE CAMOMILA)
ALOE BARBADENSIS LEAF EXTRACT (EXTRATO DA FOLHA DE ALOE VERA)
CAMELLIA SINENSIS LEAF EXTRACT (EXTRATO DA FOLHA DE CHÁ-DA-ÍNDIA)
CINNAMOMUM ZEYLANICUM BARK EXTRACT (EXTRATO DA CASCA DE CANELEIRA)
ACORUS CALAMUS ROOT EXTRACT (EXTRATO DA RAIZ DE CÁLAMO-AROMÁTICO)
COMMIPHORA MYRRHA RESIN EXTRACT (EXTRATO DA RESINA DE MIRRA)
OLEA EUROPAEA FRUIT OIL (ÓLEO DE OLIVA)
ARGANIA SPINOSA KERNEL OIL (ÓLEO DE ARGAN)
LECITHIN (LECITINA)
POLYGLYCERYL-3 DIISOSTEARATE (DIISOESTEARATO DE POLIGLICERILA-3)
GLYCERIN (GLICEROL)
GLYCERYL STEARATE (MONOESTEARATO DE GLICERILA)

ACTIVE INGREDIENT

ALUMINUM SESQUICHOLOHYDRATE

PURPOSE

ANTIPERSPIRANT

INDICATIONS AND USAGE

Shake the container well and apply to the
underarms approximately 15cm away. Protect the eyes
during the application

QUESTIONS

MAIL : SUPPORT@MYSPRAY.GROUP OR CALL (305) 766-5030

WARNINGS AND PRECAUTIONS

FLAMMABLE. DO NOT USE NEAR HEAT, FLAME OR WHILE SMOKING.
CAN CAUSE SERIOUS INJURY OR DEATH. KEEP AWAY FROM FACE AND
MOUTH TO AVOID BREATHING IN. AVOID SPRAYING IN EYES. CONTENTS
UNDER PRESSURE. DO NOT PUNCTURE OR INCINERATE. DO NOT EXPOSE
TO HEAT, SUNLIGHT OR STORE AT TEMPERATURES ABOVE 120°F/50°C
OR IN ENCLOSED PLACES THAT COULD OVERHEAT. DO NOT USE ON
BROKEN SKIN. STOP USE IF RASH OR IRRITATION OCCURS. GET MEDICAL
ATTENTION IMMEDIATELY. ASK A DOCTOR BEFORE USING IF YOU HAVE
KIDNEY DISEASE. KEEP OUT OF REACH OF CHILDREN AND ANIMALS. USE
ONLY AS DIRECTED. INTENTIONAL MISUSE BY DELIBERATELY
CONCENTRATING AND INHALING THE CONTENTS CAN BE HARMFUL OR
FATAL. AVOID THE INHALATION OF THE PRODUCT. IN CASE OF CONTACT
WITH EYES, RINSE WITH PLENTY OF WATER. IF SWALLOWED, DO NOT
INDUCE VOMITING; CONSULT YOUR HEALTHCARE PROVIDER IMMEDIATELY.
DO NOT LEAVE THE AEROSOL CONTAINER IN A VEHICLE. RISK OF LEAKAGE
AND EXPLOSION. CONTAINER MATERIAL: STEEL. BATCH AND EXPIRATION ON
THE BOTTOM OF THE CONTAINER. HELP STOP INHALATION ABUSE:
WWW.INHALANT.ORG

WARNINGS

FLAMMABLE. DO NOT USE NEAR HEAT, FLAME OR WHILE SMOKING.
CAN CAUSE SERIOUS INJURY OR DEATH. KEEP AWAY FROM FACE AND
MOUTH TO AVOID BREATHING IN. AVOID SPRAYING IN EYES. CONTENTS
UNDER PRESSURE. DO NOT PUNCTURE OR INCINERATE. DO NOT EXPOSE
TO HEAT, SUNLIGHT OR STORE AT TEMPERATURES ABOVE 120°F/50°C
OR IN ENCLOSED PLACES THAT COULD OVERHEAT. DO NOT USE ON
BROKEN SKIN. STOP USE IF RASH OR IRRITATION OCCURS. GET MEDICAL
ATTENTION IMMEDIATELY. ASK A DOCTOR BEFORE USING IF YOU HAVE
KIDNEY DISEASE. KEEP OUT OF REACH OF CHILDREN AND ANIMALS. USE
ONLY AS DIRECTED. INTENTIONAL MISUSE BY DELIBERATELY
CONCENTRATING AND INHALING THE CONTENTS CAN BE HARMFUL OR
FATAL. AVOID THE INHALATION OF THE PRODUCT. IN CASE OF CONTACT
WITH EYES, RINSE WITH PLENTY OF WATER. IF SWALLOWED, DO NOT
INDUCE VOMITING; CONSULT YOUR HEALTHCARE PROVIDER IMMEDIATELY.
DO NOT LEAVE THE AEROSOL CONTAINER IN A VEHICLE. RISK OF LEAKAGE
AND EXPLOSION. CONTAINER MATERIAL: STEEL. BATCH AND EXPIRATION ON
THE BOTTOM OF THE CONTAINER. HELP STOP INHALATION ABUSE:
WWW.INHALANT.ORG

KEEP OUT OF REACH OF CHILDREN

DOSAGE AND ADMINISTRATION

Shake the container well and apply to the
underarms approximately 15cm away. Protect the eyes
during the application